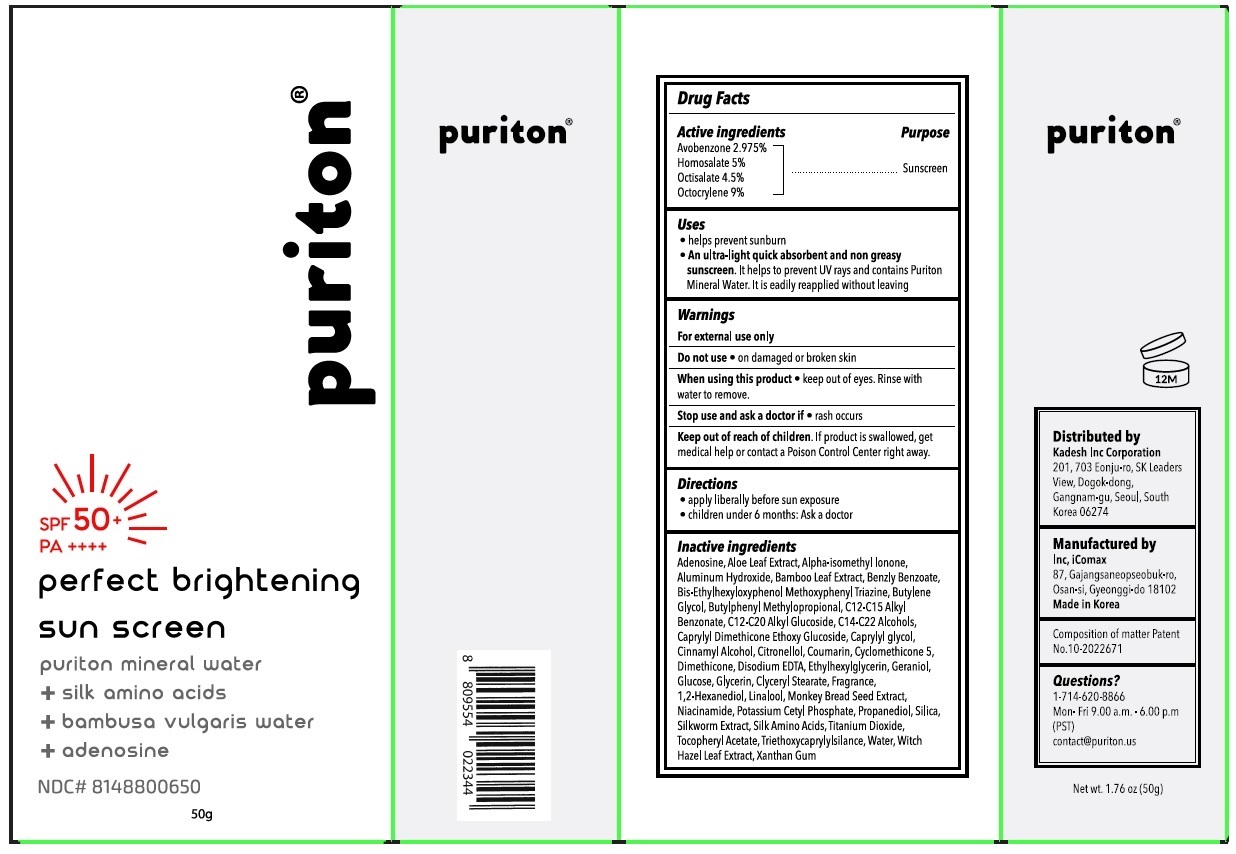 DRUG LABEL: Puriton PERFECT BRIGHTENING SUNSCREEN
NDC: 81488-006 | Form: CREAM
Manufacturer: Kadesh Incoporation Co,Ltd
Category: otc | Type: HUMAN OTC DRUG LABEL
Date: 20210318

ACTIVE INGREDIENTS: AVOBENZONE 29.75 mg/1 g; HOMOSALATE 50 mg/1 g; OCTISALATE 45 mg/1 g; OCTOCRYLENE 90 mg/1 g
INACTIVE INGREDIENTS: ADENOSINE; ALOE VERA LEAF; ISOMETHYL-.ALPHA.-IONONE; ALUMINUM HYDROXIDE; BAMBUSA VULGARIS LEAF; BENZYL BENZOATE; BEMOTRIZINOL; BUTYLENE GLYCOL; BUTYLPHENYL METHYLPROPIONAL; ALKYL (C12-15) BENZOATE; C12-20 ALKYL GLUCOSIDE; C14-22 ALCOHOLS; CAPRYLYL TRISILOXANE; CAPRYLYL GLYCOL; CINNAMYL ALCOHOL; .BETA.-CITRONELLOL, (R)-; COUMARIN; CYCLOMETHICONE 5; DIMETHICONE; EDETATE DISODIUM ANHYDROUS; ETHYLHEXYLGLYCERIN; GERANIOL; ANHYDROUS DEXTROSE; GLYCERIN; GLYCERYL MONOSTEARATE; 1,2-HEXANEDIOL; LINALOOL, (+/-)-; ADANSONIA DIGITATA SEED; NIACINAMIDE; POTASSIUM CETYL PHOSPHATE; PROPANEDIOL; SILICON DIOXIDE; BOMBYX MORI FIBER; AMINO ACIDS, SILK; TITANIUM DIOXIDE; .ALPHA.-TOCOPHEROL ACETATE; TRIETHOXYCAPRYLYLSILANE; WATER; HAMAMELIS VIRGINIANA LEAF; XANTHAN GUM

puriton® perfect brightening sun screen

Active ingredients

Avobenzone 2.975%

Homosalate 5%

Octisalate 4.5%

Octocrylene 9%

Purpose

Sunscreen

Uses

• helps prevent sunburn

• An ultra-light quick absorbent and non greasy sunscreen. It helps to prevent UV rays and contains Puriton Mineral Water. It is readily reapplied without leaving

Warnings

For external use only

Do not use • on damaged or broken skin

When using this product • keep out of eyes. Rinse with water to remove.

Stop use and ask a doctor if • rash occurs

Keep out of reach of children. If product is swallowed, get medical help or contact a Poison Control Center right away.

Directions

• apply liberally before sun exposure

• children under 6 months: Ask a doctor

Inactive ingredients

Adenosine, Aloe Leaf Extract, Alpha-isomethyl Ionone, Aluminum Hydroxide, Bamboo Leaf Extract, Benzyl Benzoate, Bis-Ethylhexyloxyphenol Methoxyphenyl Triazine, Butylene Glycol, Butylphenyl Methylpropional, C12-C15 Alkyl Benzoate, C12-C20 Alkyl Glucoside, C14-C22 Alcohols, Caprylyl Dimethicone Ethoxy Glucoside, Caprylyl glycol, Cinnamyl Alcohol, Citronellol, Coumarin, Cyclomethicone 5, Dimethicone, Disodium EDTA, Ethylhexylglycerin, Geraniol, Glucose, Glycerin, Glyceryl Stearate, Fragrance, 1,2-Hexanediol, Linalool, Monkey Bread Seed Extract, Niacinamide, Potassium Cetyl Phosphate, Propanediol, Silica, Silkworm Extract, Silk Amino Acids, Titanium Dioxide, Tocopheryl Acetate, Triethoxycaprylylsilane, Water, Witch Hazel Leaf Extract, Xanthan Gum

Questions?

1-714-620-8866

Mon-Fri 9.00 a.m. - 6.00 p.m (PST)

contact@puriton.us

SPF 50+

PA++++

puriton mineral water

+ silk amino acids

+ bambusa vulgaris water

+ adenosine

Distributed by
Kadesh Inc Corporation
201, 703 Eonju-ro, SK Leaders
View, Dogok-dong,
Gangnam-gu, Seoul, South
Korea 06274

Manufactured by
Inc, iComax
87, Gajangsaneopseobuk-ro,
Osan-si, Gyeonggi-do 18102
Made in Korea

Composition of matter Patent No. 10-2022671